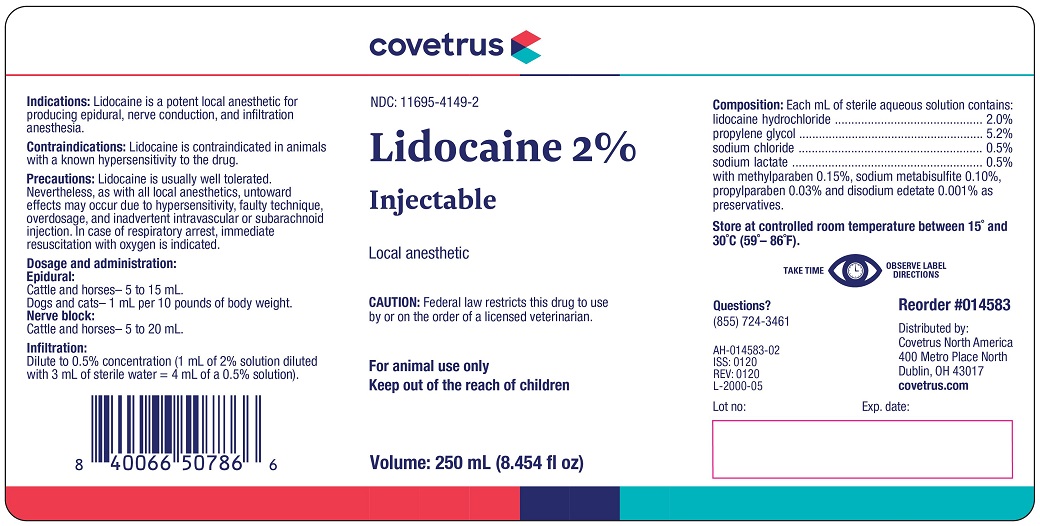 DRUG LABEL: LIDOCAINE
NDC: 11695-4149 | Form: INJECTION
Manufacturer: Covetrus North America
Category: animal | Type: PRESCRIPTION ANIMAL DRUG LABEL
Date: 20210105

ACTIVE INGREDIENTS: LIDOCAINE HYDROCHLORIDE 0.02 g/1 mL

Lidocaine 2%

INDICATIONS AND USAGE

Injectable

Local anesthetic

CAUTION: Federal law restricts this drug to use by or on the order of a licensed veterinarian.

For animal use only

Keep out of the reach of children

Indications

Lidocaine is a potent local anesthetic for producing epidural, nerve conduction, and infiltration anesthesia.

Contraindications

Lidocaine is contraindicated in animals with a known hypersensitivity to the drug.

Precautions

Lidocaine is usually well tolerated. Nevertheless, as with all local anesthetics, untoward effects may occur due to hypersensitivity, faulty technique, overdosage and inadvertent intravascular or subarachnoid injection. In case of respiratory arrest, immediate resuscitation with oxygen is indicated.

Dosage and administration

Epidural:Cattle and Horses - 5 to 15 mL
Dogs and Cats - 1 mL per 10 pounds of body weight.
Nerve Block:Cattle and Horses - 5 to 20 mL

Infiltration:Dilute to 0.5% concentration (1 mL of 2% solution diluted with 3 mL of sterile water = 4 mL of a 0.5% solution)

Composition

Each mL of sterile aqueous solution contains:
lidocaine hydrochloride........................2.0%
propylene glycol..................................5.2%
sodium chloride...................................0.5%
sodium lactate....................................0.5%
with methylparaben 0.15%, sodium metabisulfite 0.10%,
propylparaben 0.03%, and disodium edetate 0.001% as preservatives.

STORAGE AND HANDLING

Store at controlled room temperature between 15o and 30oC (59o-86oF)

TAKE TIME OBSERVE LABEL DIRECTIONS